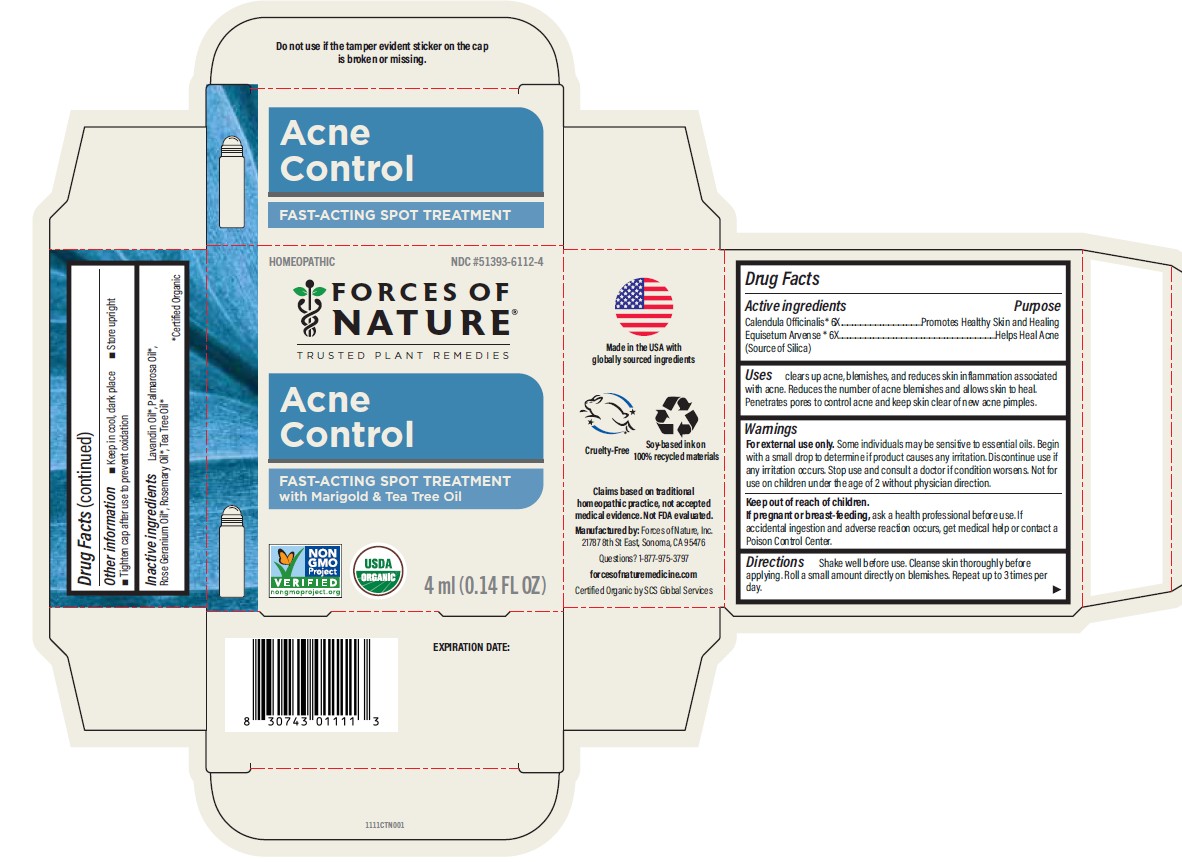 DRUG LABEL: Acne/Pimple Control
NDC: 51393-6112 | Form: SOLUTION/ DROPS
Manufacturer: Forces of Nature
Category: homeopathic | Type: HUMAN OTC DRUG LABEL
Date: 20260213

ACTIVE INGREDIENTS: CALENDULA OFFICINALIS FLOWERING TOP 6 [hp_X]/1000 mL; Silicon Dioxide 6 [hp_X]/1000 mL
INACTIVE INGREDIENTS: Lavandin Oil; Tea Tree Oil; Geranium Oil, Algerian Type; Rosemary Oil; Palmarosa Oil

Acne/Pimple Control

CONTROL DRUG FACTS

Active Ingredients

PURPOSE

Calendula Officinalis* 6X - Promotes Healthy Skin and Healing
Equisetum Arvense* 6X - Helps heal acne

(Source of Silica)

Also Contains

Lavandin Oil*, Palmarosa Oil*, Rose Geranium Oil*, Rosemary Oil*, Tea Tree Oil*

*Certified Organic

Indications

Clears up acne, blemishes, and reduces skin inflammation associated with acne. Reduces the number of acne blemishes and allows skin to heal. Penetrates pores to control acne and keep skin clear of new acne pimples.

Directions

Shake well before use. Cleanse skin thoroughly before applying. Roll a small amount directly on blemishes. Repeat up to 3 times per day.

Warnings

Some individuals may be sensitive to essential oils. Begin with a small drop to determine if the product causes any increased redness or irritation and discontinue use if it irritates your skin.

For external use only. If accidental ingestion of more than several drops, and adverse reaction occurs, get medical help or contact a Poison Control Center.

Do not apply to the eyes. If you are pregnant or breast-feeding, ask a health professional before use. Not for use on children under the age of 3.

Keep out of reach of children.

Stop use and consult a doctor if condition worsens.

Manufactured by: Forces of Nature Inc.
21787 8th St East, Sonoma, CA 95476

PRINCIPAL DISPLAY PANEL - 4 ml Bottle Box

HOMEOPATHIC

NDC #51393-6112-4

FORCES OF NATURE®

TRUSTED PLANT REMEDIES

Acne Control

FAST-ACTING SPOT TREATMENT

with Marigold & Tea Tree Oil

Non-GMO Project Verified

nongmoproject.org

USDA Organic

4 ml (0.14 FL OZ)

Add image transcription here...